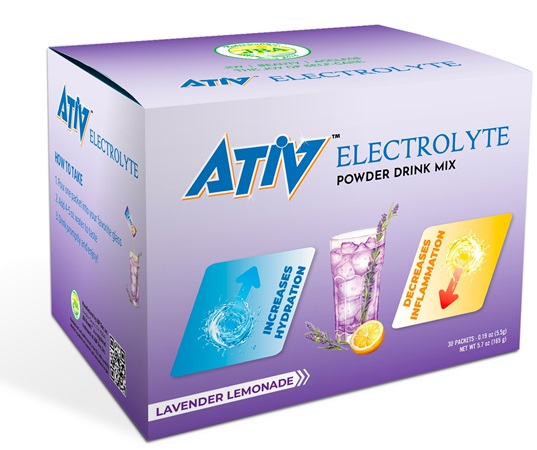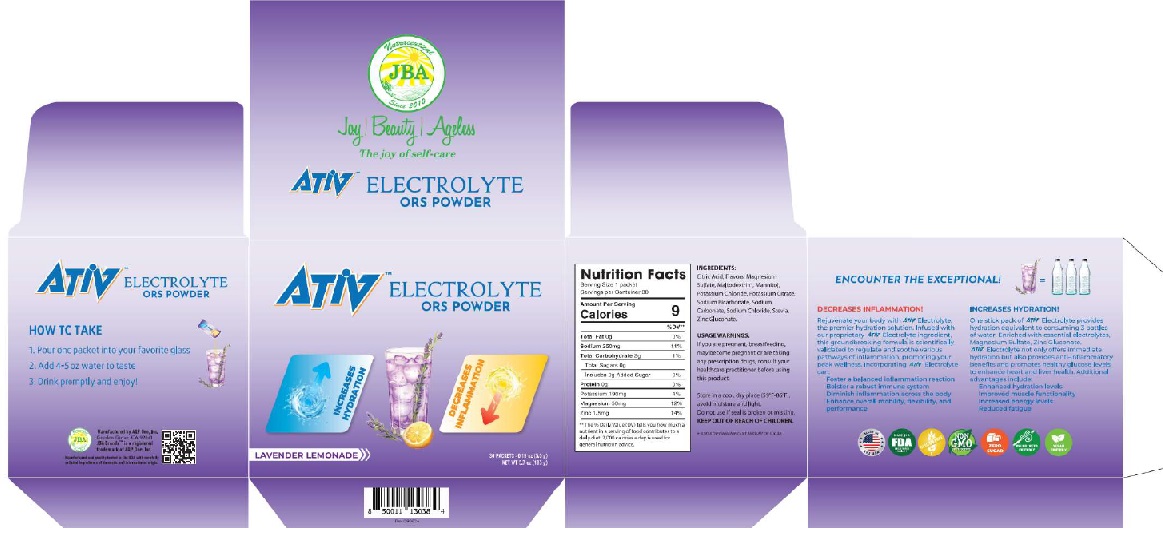 DRUG LABEL: JBA ATIV ELECTROLYTE ORS LAVENDER LEMONADE
NDC: 13411-868 | Form: POWDER
Manufacturer: Advanced Pharmaceutical Services, Inc. Dba Affordable Quality Pharmaceuticals
Category: otc | Type: HUMAN OTC DRUG LABEL
Date: 20251128

ACTIVE INGREDIENTS: POTASSIUM 190 mg/1 1; MAGNESIUM 50 mg/1 1; ZINC 10 mg/1 1
INACTIVE INGREDIENTS: ANHYDROUS CITRIC ACID; MALTODEXTRIN; MANNITOL; STEVIA REBAUDIANA LEAF

Identity

Nutrition Supplement

Direction

1. Pour one packet into your favorite glass
2. Add 4-5 oz water of taste
3. Drink promptly and enjoy!

Safe handling warning

JBA ATIV ELECTROLYTE ORS POWDER

ENCOUNTER THE EXCEPTIONAL!

DECREASES INFLAMMATION

Rejuvenate your body with ATIV Electrolyte, the premier hydration solution. Infused with our proprietary ATIV Electrolyte ingredient, this groundbreaking formula is scientifically validated to regulate and soothe various pathways of inflammation, promoting your peak wellness. Incorporating ATIV Electrolyte can:
Foster a balanced inflammation reaction
Bolster a robust immune system
Diminish inflammation across the body
Enhance overall mobility, flexibility, and performance

INCREASES HYDRATION

One stick pack of ATIV Electrolyte provides hydration equivalent to consuming 3 bottles of water. Enriched with essential electrolytes, Magnesium Sulfate, Zinc Gluconate.
ATIV Electrolyte not only offers immediate hydration but also provides anti-inflammatory benefits and promotes healthy glucose levels to enhance heart and liver health. Additional advantages include:
Enhanced hydration levels
Improved muscle functionality
Increased energy levels
Reduced fatigue

WARNINGS

Other Ingredients

Citric Acid, Flavors, Maltodextrin, Mannitol, Stevia